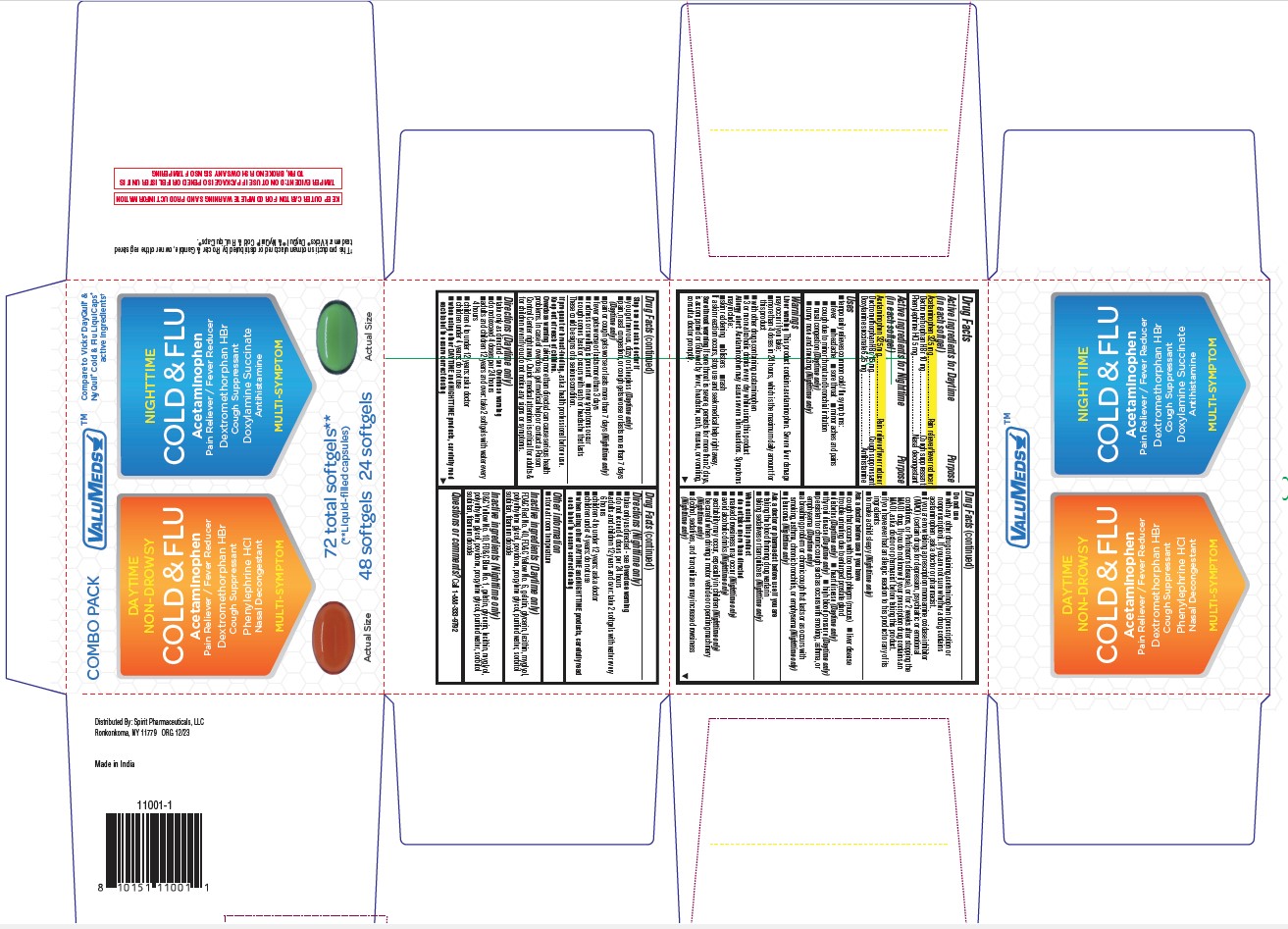 DRUG LABEL: Daytime Non Drowsy Cold and Flu and Nighttime Cold and flu
NDC: 68210-5030 | Form: KIT | Route: ORAL
Manufacturer: Spirit Pharmaceuticals LLC
Category: otc | Type: HUMAN OTC DRUG LABEL
Date: 20241213

ACTIVE INGREDIENTS: ACETAMINOPHEN 325 mg/1 1; DEXTROMETHORPHAN HYDROBROMIDE 10 mg/1 1; PHENYLEPHRINE HYDROCHLORIDE 5 mg/1 1; ACETAMINOPHEN 325 mg/1 1; DEXTROMETHORPHAN HYDROBROMIDE 15 mg/1 1; DOXYLAMINE SUCCINATE 6.25 mg/1 1
INACTIVE INGREDIENTS: FD&C RED NO. 40; FD&C YELLOW NO. 6; GELATIN; GLYCERIN; LECITHIN, SOYBEAN; MEDIUM-CHAIN TRIGLYCERIDES; POLYETHYLENE GLYCOL 400; POVIDONE; PROPYLENE GLYCOL; WATER; SORBITOL; TITANIUM DIOXIDE; D&C YELLOW NO. 10; FD&C BLUE NO. 1; GELATIN; GLYCERIN; LECITHIN, SOYBEAN; MEDIUM-CHAIN TRIGLYCERIDES; POLYETHYLENE GLYCOL 400; POVIDONE; PROPYLENE GLYCOL; WATER; SORBITOL; TITANIUM DIOXIDE

Daytime Non Drowsy Cold and Flu and Nighttime Cold and Flu

Uses

- temporarily relieves common cold/flu symptoms:
- fever
- headache
- sore throat
- minor aches and pain
- cough due to minor throat and bronchial iffitation
- nasal congestion (Daytime only)
- runny nose and sneezing (Nighttime only)

Warnings

Liver warningThis product contains acetaminophen. Severe liver damage may occur if you take: ● more than 4 doses in 24 hours, which is the
maximum daily amount for this product ● with other drugs containing acetaminophen ● 3 or more alcoholic drinks every day while using this product

Allergy alert:Acetaminophen may cause severe skin reactions.
Symptoms may include: ● skin reddening ● blisters ● rash
If a skin reaction occurs, stop use and seek medical help right away.

Sore throat warningIf sore throat is severe, persists for more than 2 days, is accompanied or followed by fever, headache, rash, nausea, or vomiting, consult a doctor promptly.

Do not use

● with any other drug containing acetaminophen (prescription or nonprescription). If you are not sure whether a drug contains
acetaminophen, ask a doctor or pharmacist.

● if you are now taking a prescription monoamine oxidase inhibitor (MAOI) (certain drugs for depression, psychiatric or emotional conditions, or Parkinson's disease), or for 2 weeks after stopping the MAOI drug. If you do not know if your prescription drug contains an MAOI, ask a doctor or pharmacist before taking this product.

● if you have ever had an allergic reaction to this product or any of its ingredients

● to make a child sleepy (Nighttime only)

Ask a doctor before use if you have

● cough that occurs with too much phlegm (mucus) ● liver disease
● trouble urinating due to enlarged prostate gland
● diabetes (Daytime only) ● heart disease (Daytime only)
● thyroid disease (Daytime only) ● high blood pressure (Daytime only)
● persistent or chronic cough such as occurs with smoking, asthma, or emphysema (Daytime only)
● a breathing problem or chronic cough that lasts or as occurs with smoking, asthma, chronic bronchitis, or emphysema (Nighttime only)
● glaucoma (Nighttime only)

Ask a doctor or pharmacist before use if you are

● taking the blood thinning drug warfarin
● taking sedatives or tranquilizers (Nighttime only)

Stop use and ask a doctor if

● you get nervous, dizzy or sleepless (Daytime only)
● pain, nasal congestion, or cough gets worse or lasts more than 7 days (Daytime only)
● pain or cough gets worse or lasts more than 7 days (Nighttime only)
● fever gets worse or lasts more than 3 days
● redness or swelling is present
● new symptoms occur
● cough comes back or occurs with rash or headache that lasts
These could be signs of a serious condition.

Keep out of reach of children.

OVERDOSAGE

Overdose warningTaking more than directed can cause serious health problems. In case of overdose, get medical help or contact a Poison Control Center right away. Quick medical attention is critical for adults & for children even if you do not notice any signs or symptoms.

Other information

- store at room temperature.

Inactive ingredients

DAYTIME

FD&C Red# 40, FD&C Yellow# 6, gelatin, glycerin, polyethylene glycol, lecithin, myglyol, povidone, propylene glycol, purified water, sorbitol sorbitan, titanium dioxide

NIGHTTIME

D&C Yellow# 10, FD&C Blue# 1, gelatin, glycerin, myglyol, lecithin, polyethylene glycol, povidone, propylene glycol, purified water, sorbitol sorbitan, polysorb, sorbitol sorbitan, titanium dioxide

Questions or comments?

1-888-333-9792